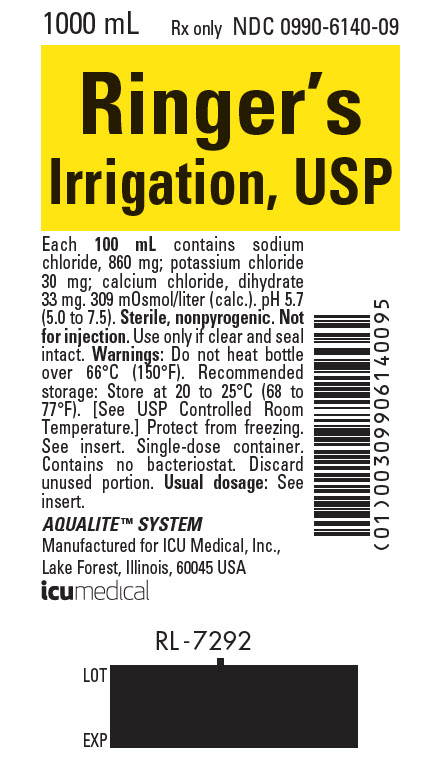 DRUG LABEL: Ringers Irrigation
NDC: 0990-6140 | Form: INJECTION, SOLUTION
Manufacturer: ICU Medical Inc.
Category: prescription | Type: HUMAN PRESCRIPTION DRUG LABEL
Date: 20210914

ACTIVE INGREDIENTS: SODIUM CHLORIDE 860 mg/100 mL; POTASSIUM CHLORIDE 30 mg/100 mL; CALCIUM CHLORIDE 33 mg/100 mL
INACTIVE INGREDIENTS: WATER

Ringer's Irrigation, USP

FOR ALL GENERAL IRRIGATION, WASHING AND RINSING PURPOSES

Not For Injection By Usual Parenteral Routes

Semi-rigid Irrigation Container

Rx only

DESCRIPTION

These products are sterile, nonpyrogenic solutions of electrolytes in water for injection intended only for sterile irrigation, washing and rinsing purposes.

Each 100 mL of Ringer’s Irrigation, USP contains: Sodium chloride 860 mg; potassium chloride 30 mg; calcium chloride dihydrate 33 mg. The pH is 5.7 (5.0 — 7.5). The solution is isotonic (309 mOsmol/liter, calc.) and has the following electrolyte content (mEq/liter): Na^+ 147.5; K^+ 4; Ca^++ 4.5; Cl^− 156.

The solution contains no bacteriostat, antimicrobial agent or added buffer and is intended only for use as single-dose or short procedure irrigation. When smaller volumes are required the unused portion should be discarded. Ringer’s Irrigation, USP may be classified as a sterile irrigant, wash, rinse and pharmaceutical vehicle.

Calcium Chloride, USP is chemically designated calcium chloride dihydrate (CaCl2 • 2H2O), white fragments or granules freely soluble in water.

Potassium Chloride, USP is chemically designated KCl, a white granular powder freely soluble in water.

Sodium Chloride, USP is chemically designated NaCl, a white crystalline powder freely soluble in water.

Water for Injection, USP is chemically designated H2O.

The semi-rigid container is fabricated from a specially formulated polyolefin. It is a copolymer of ethylene and propylene. The container requires no vapor barrier to maintain the proper drug concentration.

Solutions in contact with the plastic container may leach out certain chemical components from the plastic in very small amounts; however, biological testing was supportive of the safety of the plastic container materials.

Exposure to temperatures above 25°C/77°F during transport and storage will lead to minor losses in moisture content. Higher temperatures lead to greater losses. It is unlikely that these minor losses will lead to clinically significant changes within the expiration period.

CLINICAL PHARMACOLOGY

Ringer’s Irrigation, USP exerts a mechanical cleansing action for sterile irrigation of body cavities, tissues or wounds, indwelling urethral catheters and surgical drainage tubes, and for washing, rinsing or soaking surgical dressings, instruments and laboratory specimens. It also serves as a vehicle for drugs used for irrigation or other pharmaceutical preparations.

Ringer’s Irrigation, USP provides an isotonic irrigation with the same ionic constituents as Ringer’s Injection, USP, a modification of Ringer’s solution (also called Ringer’s mixture) originally used only as a topical physiologic salt solution.

Ringer’s Irrigation, USP is considered generally compatible with living tissues and organs.

Calcium Chloride in water dissociates to provide calcium (Ca^++) and chloride (Cl^−) ions. They are normal constituents of the body fluids and are dependent on various physiologic mechanisms for maintenance of balance between intake and output. Approximately 80% of body calcium is excreted in the feces as insoluble salts; urinary excretion accounts for the remaining 20%.

Potassium chloride in water dissociates to provide potassium (K^+) and chloride (Cl^−) ions. Potassium is the chief cation of body cells (160 mEq/liter of intracellular water). It is found in low concentration in plasma and extracellular fluids (3.5 to 5.0 mEq/liter in a healthy adult). Potassium plays an important role in electrolyte balance.

Normally about 80 to 90% of the potassium intake is excreted in the urine; the remainder in the stools and to a small extent, in the perspiration. The kidney does not conserve potassium well so that during fasting or in patients on a potassium free diet, potassium loss from the body continues resulting in potassium depletion.

Sodium chloride in water dissociates to provide sodium (Na^+) and chloride (Cl^−) ions. Sodium (Na^+) is the principal cation of the extracellular fluid and plays a large part in the therapy of fluid and electrolyte disturbances. Chloride (Cl^−) has an integral role in buffering action when oxygen and carbon dioxide exchange occurs in the red blood cells. The distribution and excretion of sodium (Na^+) and chloride (Cl^−) are largely under the control of the kidney which maintains a balance between intake and output.

Water is an essential constituent of all body tissues and accounts for approximately 70% of total body weight. Average normal adult daily requirement ranges from two to three liters (1.0 to 1.5 liters each for insensible water loss by perspiration and urine production).

Water balance is maintained by various regulatory mechanisms. Water distribution depends primarily on the concentration of electrolytes in the body compartments and sodium (Na^+) plays a major role in maintaining physiologic equilibrium.

INDICATIONS AND USAGE

Ringer’s Irrigation, USP is indicated for all general irrigation, washing and rinsing purposes which permit use of a sterile, nonpyrogenic electrolyte solution.

CONTRAINDICATIONS

NOT FOR INJECTION BY USUAL PARENTERAL ROUTES.

An electrolyte solution should not be used for irrigation during electrosurgical procedures.

WARNINGS

FOR IRRIGATION ONLY. NOT FOR INJECTION.

Irrigating fluids have been demonstrated to enter the systemic circulation in relatively large volumes; thus this irrigation must be regarded as a systemic drug. Absorption of large amounts can cause fluid and/or solute overloading resulting in dilution of serum electrolyte concentrations, overhydration, congested states or pulmonary edema.

The risk of dilutional states is inversely proportional to the electrolyte concentrations of administered parenteral solutions. The risk of solute overload causing congested states with peripheral and pulmonary edema is directly proportional to the electrolyte concentrations of such solutions.

Do not heat over 66° C (150° F).

PRECAUTIONS

Do not use for irrigation that may result in absorption into the blood.

Caution should be observed when the solution is used for continuous irrigation or allowed to “dwell” inside body cavities because of possible absorption into the blood stream and the production of circulatory overload.

Aseptic technique is essential with the use of sterile solutions for irrigation of body cavities, wounds and urethral catheters or for wetting dressings that come in contact with body tissues.

When used as a “pour” irrigation, no part of the contents should be allowed to contact the surface below the outer protected thread area of the semi-rigid wide mouth container. When used for irrigation via irrigation equipment, the administration set should be attached promptly. Unused portions should be discarded and a fresh container of appropriate size used for the start-up of each cycle or repeat procedure. For repeated irrigations of urethral catheters, a separate container should be used for each patient.

Do not administer unless solution is clear, seal is intact and container is undamaged. Discard unused portion.

Drug Interactions

Additives may be incompatible. Consult with pharmacist, if available. When introducing additives, use aseptic technique, mix thoroughly and do not store.

Carcinogenesis, Mutagenesis, Impairment of Fertility:

Studies with Ringer’s Irrigation, USP have not been performed to evaluate carcinogenic potential, mutagenic potential, or effects on fertility.

Nursing Mothers:

Caution should be exercised when Ringer’s Irrigation, USP is administered to a nursing woman.

Pregnancy:

Teratogenic Effects.

Pregnancy Category C. Animal reproduction studies have not been conducted with Ringer’s Irrigation, USP. It is also not known whether Ringer’s Irrigation, USP can cause fetal harm when administered to a pregnant woman or can affect reproduction capacity. Ringer’s Irrigation, USP should be given to a pregnant woman only if clearly needed.

Pediatric Use:

Safety and effectiveness in pediatric patients have not been established.

Geriatric Use:

Clinical studies of Ringer’s Irrigation have not been performed to determine whether patients over 65 years respond differently from younger subjects. Other reported clinical experience has not identified differences in responses between elderly and younger patients. In general, dose selection for an elderly patient should be cautious, reflecting the greater frequency of decreased hepatic, renal, or cardiac function, and of concomitant disease or other drug therapy.

This drug is known to be substantially excreted by the kidney, and the risk of toxic reactions to this drug may be greater in patients with impaired renal function. Because elderly patients are more likely to have decreased renal function, care should be taken in dose selection, and it may be useful to monitor renal function.

ADVERSE REACTIONS

Possible adverse effects arising from the irrigation of body cavities, tissues, or indwelling catheters and tubes are usually avoidable when proper procedures are followed. Displaced catheters or drainage tubes can lead to irrigation or infiltration of unintended structures or cavities. Excessive volume or pressure during irrigation of closed cavities may cause undue distention or disruption of tissues. Accidental contamination from careless technique may transmit infection. Should any adverse reaction occur, discontinue the irrigant, evaluate the patient, institute appropriate therapeutic countermeasures and save the remainder of the fluid for examination if deemed necessary.

OVERDOSAGE

In the event of overhydration or solute overload, re-evaluate the patient and institute appropriate corrective measures. (See WARNINGS, PRECAUTIONS and ADVERSE REACTIONS.)

DOSAGE AND ADMINISTRATION

The dose is dependent upon the capacity or surface area of the structure to be irrigated and the nature of the procedure. When used as a vehicle for other drugs, the manufacturer’s recommendations should be followed.

Parenteral drug products should be inspected visually for particulate matter and discoloration prior to administration, whenever solution container permits. (See PRECAUTIONS.)

HOW SUPPLIED

Ringer’s Irrigation, USP is supplied in a single-dose 1000 mL semi-rigid irrigation container (NDC No. 0409–6140–09; NDC No. 0990-6140-09).

ICU Medical is transitioning NDC codes from the "0409" to a "0990" labeler code. Both NDC codes are expected to be in the market for a period of time.

Store at 20 to 25°C (68 to 77°F). [See USP Controlled Room Temperature.] Protect from freezing.

Revised: July, 2020

EN-5962

Manufactured for ICU Medical, Inc., Lake Forest, Illinois, 60045, USA

PRINCIPAL DISPLAY PANEL - 1000 mL Bottle Label

1000 mL
Rx only
NDC 0990-6140-09

Ringer's
Irrigation, USP

100 mL contains sodium
chloride, 860 mg; potassium chloride
30 mg; calcium chloride, dihydrate
33 mg. 309 mOsmol/liter (calc.). pH 5.7
(5.0 to 7.5). Sterile, nonpyrogenic. Not
for injection. Use only if clear and seal
intact. Warnings: Do not heat bottle
over 66°C (150°F). Recommended
storage: Store at 20 to 25°C (68 to
77°F). [See USP Controlled Room
Temperature.] Protect from freezing.
See insert. Single-dose container.
Contains no bacteriostat. Discard
unused portion. Usual dosage: See
insert.

AQUALITE™ SYSTEM
Manufactured for ICU Medical, Inc.,
Lake Forest, Illinois, 60045 USA
icumedical

RL -7292

LOT
EXP